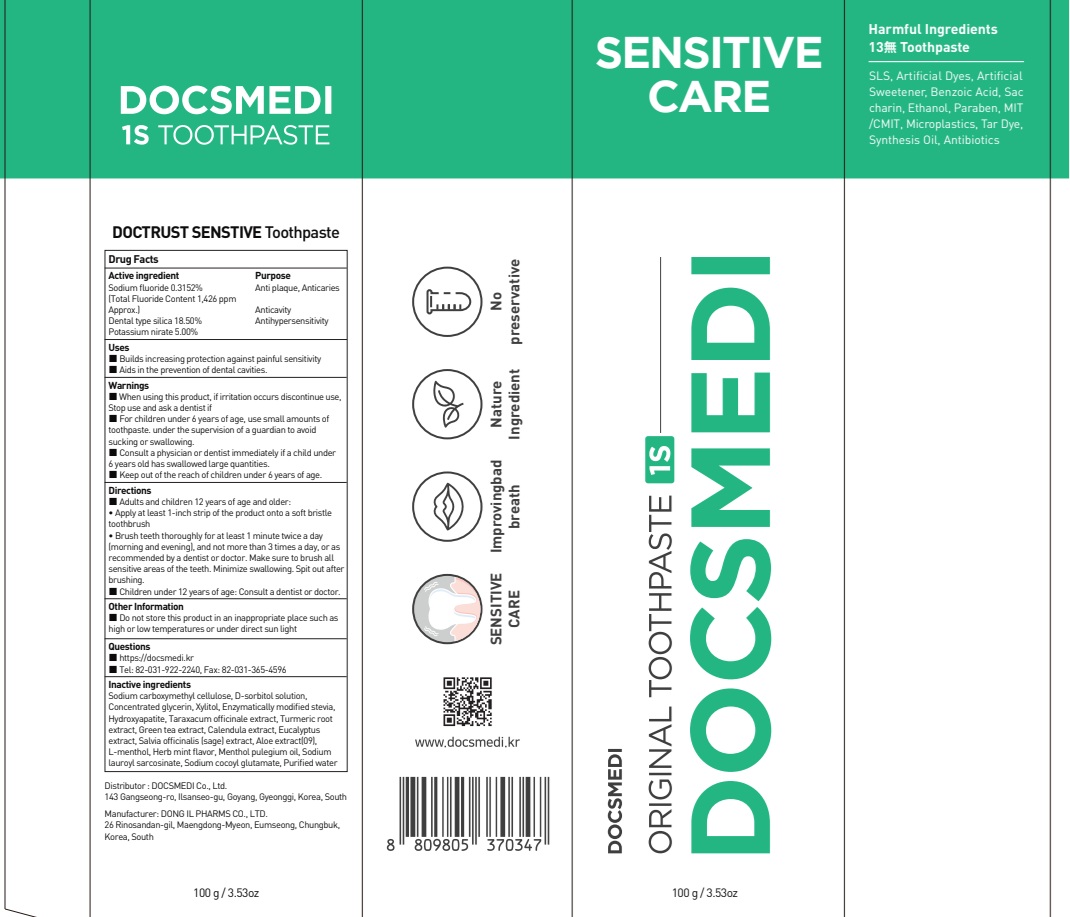 DRUG LABEL: DOCTRUST ONE S Tooth
NDC: 73242-1124 | Form: PASTE, DENTIFRICE
Manufacturer: DONG IL PHARMS CO.,LTD
Category: otc | Type: HUMAN OTC DRUG LABEL
Date: 20251125

ACTIVE INGREDIENTS: SODIUM FLUORIDE 0.31 g/100 g; SILICON DIOXIDE 18.5 g/100 g; POTASSIUM NITRATE 5 g/100 g
INACTIVE INGREDIENTS: CARBOXYMETHYLCELLULOSE SODIUM, UNSPECIFIED; SORBITOL

ACTIVE INGREDIENT

Sodium fluoride 0.3152%
(Total Fluoride Content 1,426 ppm Approx.)
Dental type silica 18.50%
Potassium nirate 5.00%

INACTIVE INGREDIENTS

Sodium carboxymethyl cellulose, D-sorbitol solution, Concentrated glycerin, Xylitol, Enzymatically modified stevia, Hydroxyapatite, Taraxacum officinale extract, Turmeric root extract, Green tea extract, Calendula extract, Eucalyptus extract, Salvia officinalis (sage) extract, Aloe extract(09), L-menthol, Herb mint flavor, Cooling flavor, Menthol pulegium oil, Sodium lauroyl sarcosinate, Sodium cocoyl glutamate, Purified water

PURPOSE

Anti plaque, Anticaries, Anticavity, Antihypersensitivity

WARNINGS

■ When using this product, if irritation occurs discontinue use, Stop use and ask a dentist if
■ For children under 6 years of age, use small amounts of toothpaste.
under the supervision of a guardian to avoid sucking or swallowing.
■ Consult a physician or dentist immediately if a child under 6 years old has swallowed large quantities.
■ Keep out of the reach of children under 6 years of age.

KEEP OUT OF REACH OF CHILDREN

■ Keep out of the reach of children under 6 years of age.

Uses

■ Builds increasing protection against painful sensitivity
■ Aids in the prevention of dental cavities.

Directions

■ Adults and children 12 years of age and older:
• Apply at least 1-inch strip of the product onto a soft bristle toothbrush
• Brush teeth thoroughly for at least 1 minute twice a day (morning and evening), and not more than 3 times a day, or as recommended by a dentist or doctor. Make sure to brush all sensitive areas of the teeth. Minimize swallowing. Spit out after brushing.
■ Children under 12 years of age: Consult a dentist or doctor.

Other Information

■ Do not store this product in an inappropriate place such as high or low temperatures or under direct sun light

Questions

https://docsmedi.kr
Tel: 82-031-922-2240, Fax: 82-43-883-2844